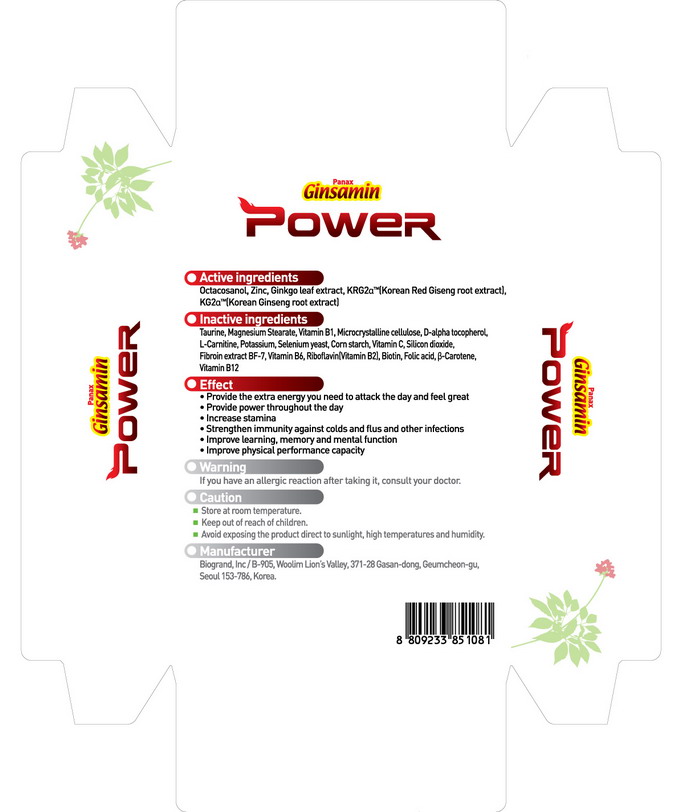 DRUG LABEL: Ginsamin Power
NDC: 44738-8001 | Form: TABLET
Manufacturer: Biogrand Co., Ltd
Category: otc | Type: HUMAN OTC DRUG LABEL
Date: 20100307

ACTIVE INGREDIENTS: GINKGO 80.4 mg/1 1; ASIAN GINSENG 118.2 mg/1 1; 1-OCTACOSANOL 3 mg/1 1; ZINC 5.4 mg/1 1

Drug Facts

ACTIVE INGREDIENT

Active Ingredients: Ginkgo leaf extract, Korean ginseng root extract, Octacosanol, Zinc

Drug Facts
Product name:
Ginsamin Power
Active ingredients
Ginkgo leaf extract, Korean ginseng root extract, Octacosanol, Zinc
Inactive ingredients
vitamin B1, riboflavin, vitamin B6, vitamin B12, vitamin C, cellulose,
D-alpha tocopherol, B-carotene, L-carnitine, corn starch, biotin, folic acid,
taurine, selenium yeast, magnesium stearate, silicon dioxide
Effect
• strengthen immunity against colds and flus and other infections
• improve learning, memory and mental function
• improve physical performance capacity
Warning
If you have an allergic reaction after taking it, consult your doctor
Caution
• Store at room temperature.
• Keep out of reach of children.
• Avoid exposing the product direct to sunlight, high temperatures and humidity.
• Manufacturer
Manufacturer
Biogrand, lnc / B-905, Woolim Lion’s Valley, 371-28 Gasan-dong, Geumcheon-gu, Seoul 153-786, Korea